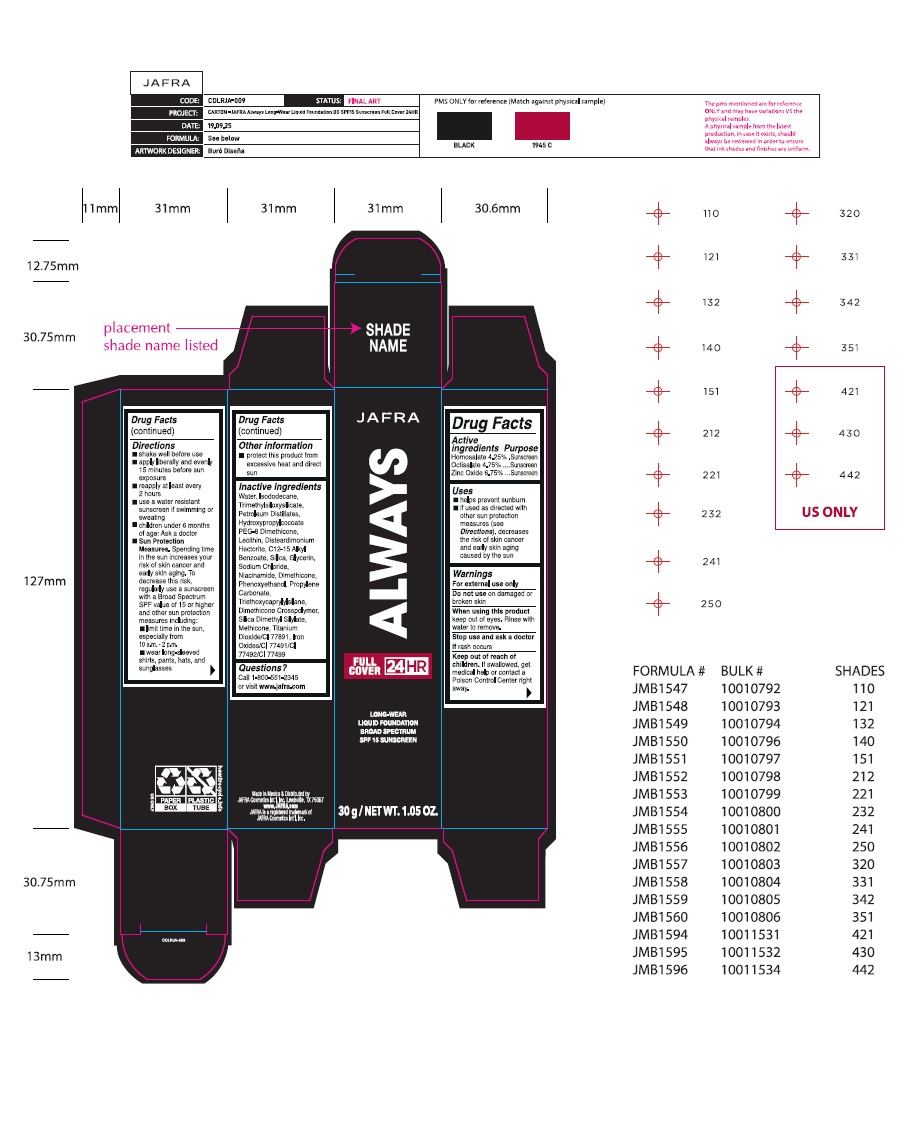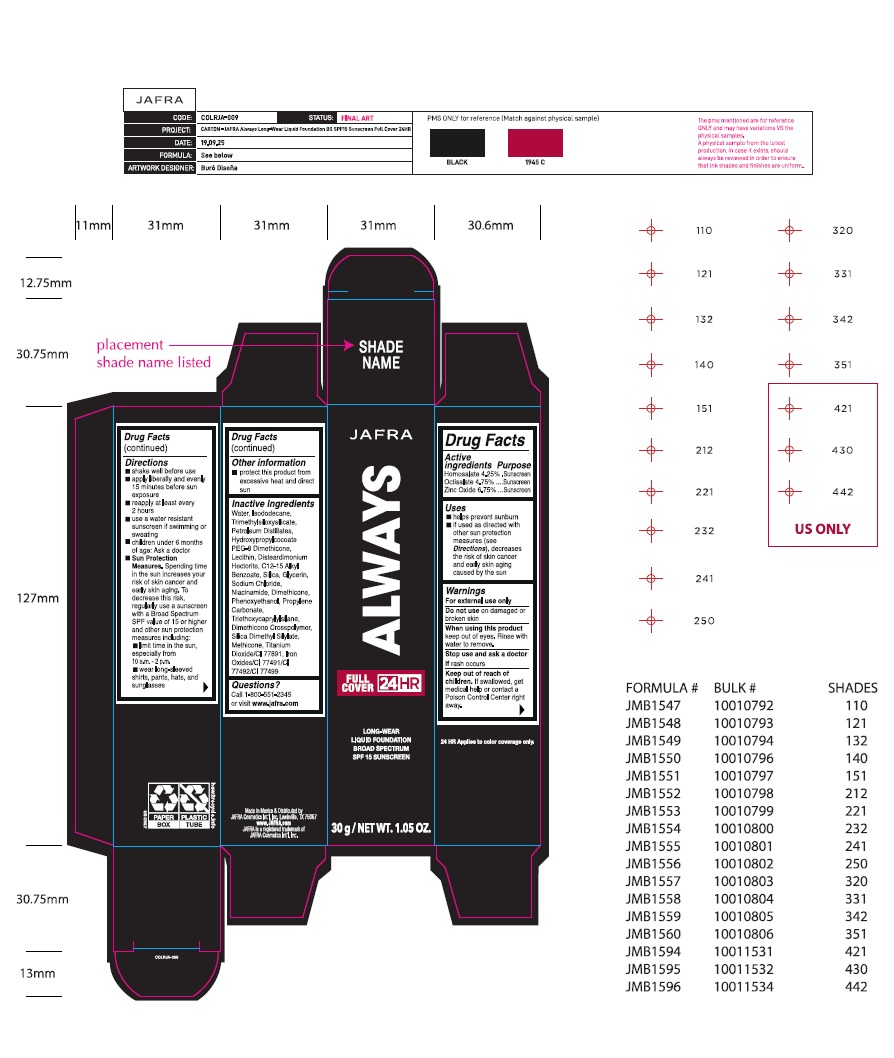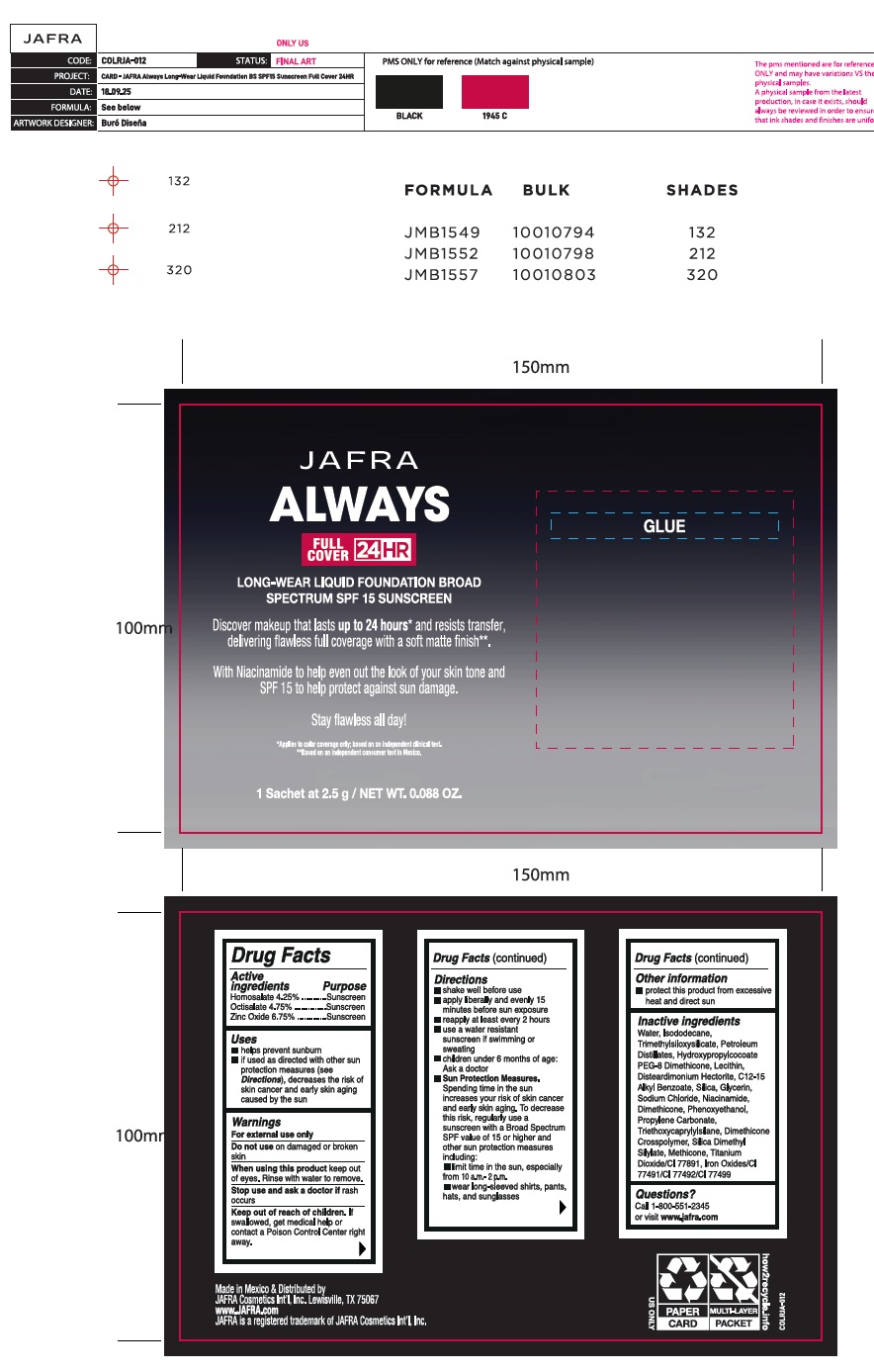 DRUG LABEL: JAFRA ALWAYS LONG WEAR FOUNDATION BROAD SPECTRUM SPF 15 SUNSCREEN 320
NDC: 68828-320 | Form: LIQUID
Manufacturer: Distribuidora Comercial Jafra, S.A. de C.V.
Category: otc | Type: HUMAN OTC DRUG LABEL
Date: 20260123

ACTIVE INGREDIENTS: HOMOSALATE 4.25 g/100 g; OCTISALATE 4.75 g/100 g; ZINC OXIDE 6.75 g/100 g
INACTIVE INGREDIENTS: WATER; ISODODECANE; TRIMETHYLSILOXYSILICATE (M/Q 0.6-0.8); C13-14 ISOPARAFFIN; HYDROXYPROPYLCOCOATE PEG-8 DIMETHICONE; SOYBEAN LECITHIN; DISTEARDIMONIUM HECTORITE; ALKYL (C12-15) BENZOATE; SILICON DIOXIDE; GLYCERIN; SODIUM CHLORIDE; NIACINAMIDE; DIMETHICONE, UNSPECIFIED; PHENOXYETHANOL; PROPYLENE CARBONATE; TRIETHOXYCAPRYLYLSILANE; DIMETHICONE CROSSPOLYMER (450000 MPA.S); SILICA DIMETHYL SILYLATE; METHICONE (20 CST); TITANIUM DIOXIDE; FERRIC OXIDE YELLOW; FERRIC OXIDE RED; FERROSOFERRIC OXIDE

Active ingredients Purpose

Homosalate 4.25% Sunscreen

Octisalate 4.75% Sunscreen

Zinc Oxide 6.75% Sunscreen

Uses

- helps prevent sunburn
- if used as directed with other sun protection measures (see Directions), decreases the risk of skin cancer and early skin aging caused by the sun

Warnings

For external use only
Do not useon damaged or broken skin
When using this productkeep out of eyes. Rinse with water to remove.
Stop use and ask a doctor ifrash occurs
Keep out of reach of children. If swallowed, get medical help or contact a Poison Control Center right away.

Directions

- shake well before use
- apply liberally and evenly 15 minutes before sun exposure
- reapply at least every 2 hours
- use a water resistant sunscreen if swimming or sweating
- children under 6 months of age: Ask a doctor
- Sun Protection Measures. Spending time in the sun increases your risk of skin cancer and early skin aging. To decrease this risk, regularly use a sunscreen with a Broad Spectrum SPF value of 15 or higher and other sun protection measures including:

•limit time in the sun, especially from 10 a.m. - 2 p.m.
•wear long-sleeved shirts, pants, hats, and sunglasses

Other information

- protect this product from excessive heat and direct sun

Inactive ingredients

Water, Isododecane, Trimethylsiloxysilicate, Petroleum Distillates, Hydroxypropylcocoate PEG-8 Dimethicone, Lecithin, Disteardimonium Hectorite, C12-15 Alkyl Benzoate, Silica, Glycerin, Sodium Chloride, Niacinamide, Dimethicone, Phenoxyethanol, Propylene Carbonate, Triethoxycaprylylsilane, Dimethicone Crosspolymer, Silica Dimethyl Silylate, Methicone, Titanium Dioxide/CI 77891, Iron Oxides/CI 77491/CI 77492/CI 77499

Questions?

Call 1-800-551-2345 or visit www.jafra.com